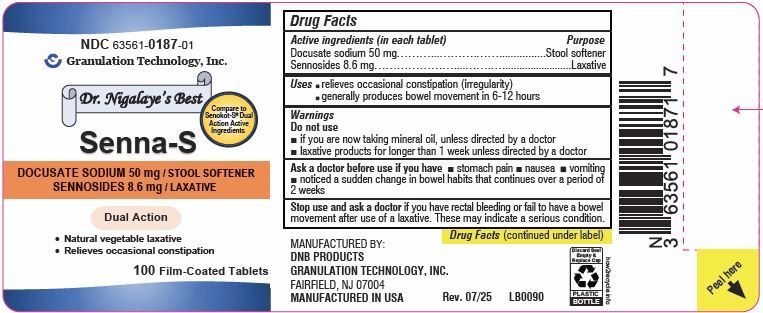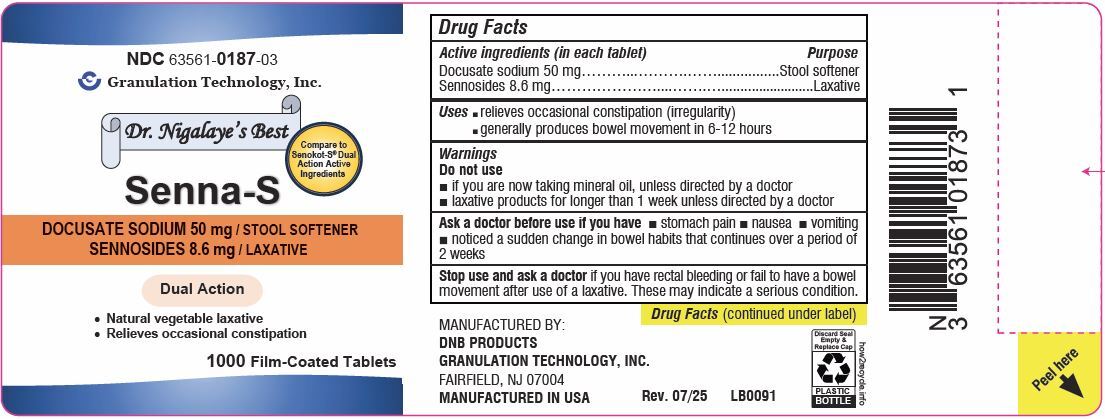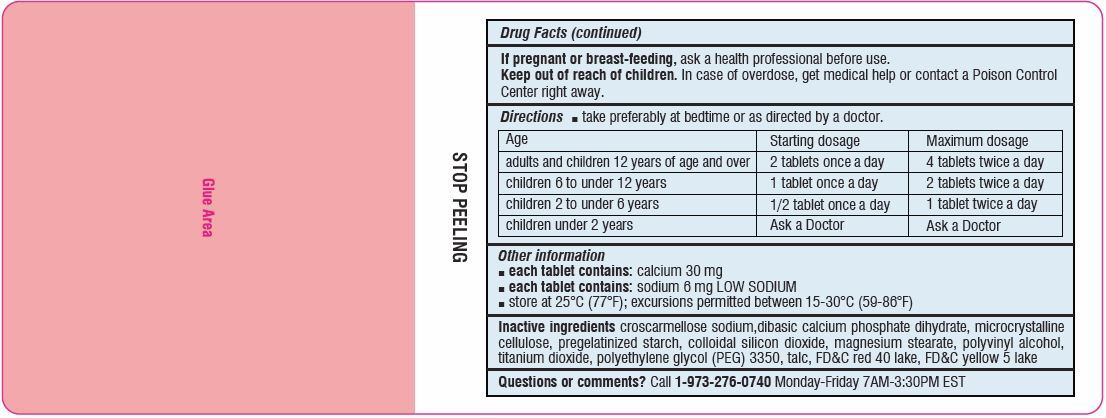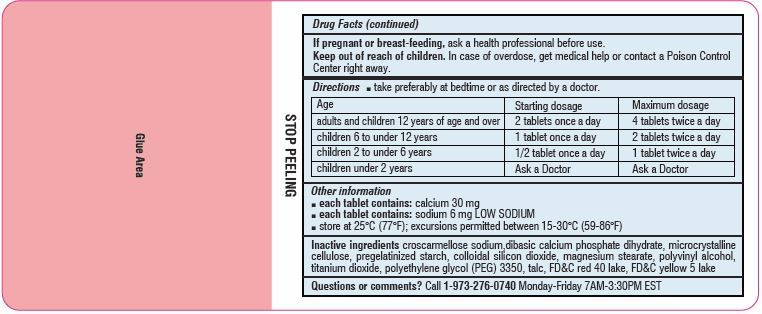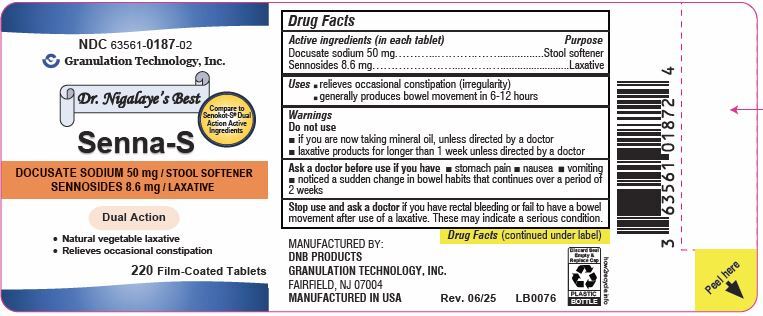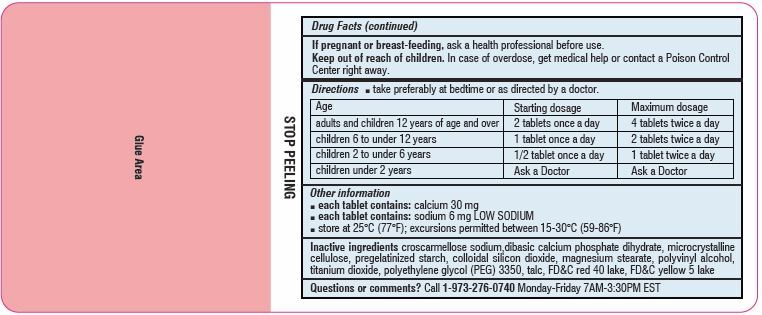 DRUG LABEL: Senna-S
NDC: 63561-0187 | Form: TABLET, FILM COATED
Manufacturer: Granulation Technology, Inc.
Category: otc | Type: HUMAN OTC DRUG LABEL
Date: 20250730

ACTIVE INGREDIENTS: SENNOSIDES 8.6 mg/1 1; DOCUSATE SODIUM 50 mg/1 1
INACTIVE INGREDIENTS: CROSCARMELLOSE SODIUM; DIBASIC CALCIUM PHOSPHATE DIHYDRATE; MICROCRYSTALLINE CELLULOSE 200; STARCH, CORN; SILICON DIOXIDE; MAGNESIUM STEARATE; POLYVINYL ALCOHOL; TITANIUM DIOXIDE; POLYETHYLENE GLYCOL 3350; TALC; FD&C RED NO. 40 ALUMINUM LAKE; FD&C YELLOW NO. 5 ALUMINUM LAKE

SENNA-S
DOCUSATE SODIUM 50 mg / STOOL SOFTENER
SENNOSIDES 8.6 mg / LAXATIVE

Active ingredients (in each tablet)

Docusate Sodium         50 mg

Sennosides                       8.6 mg

Purpose

Stool softener

Laxative

Uses

- Relieves occasional constipation (irregularity)
- Generally produces a bowel movement in 6-12 hours

Do not use

- If you are now taking mineral oil, unless directed by a doctor
- Laxative products for longer than one week unless directed by a doctor

Ask a doctor before use if you have

- Stomach pain
- Nausea
- Vomiting
- Noticed a sudden change in bowel habits that continues over a period of two weeks

Stop using and ask a doctor if

you have rectal bleeding or fail to have a bowel movement after use of a laxative. These may indicate a serious condition.

If pregnant or breast-feeding,

ask a health professional before use.

Keep out of reach of children.

In case of overdose, get medical help or contact a Poison Control Center (1-800-222-1222) right away.

Directions

- Take preferably at bedtime or as directed by a doctor

age | starting dosage | maximum dosage
adults and children 12 years of age and over | 2 tablets once a day | 4 tablets twice a day
children 6 to under 12 years | 1 tablet once a day | 2 tablets twice a day
children 2 to under 6 years | 1/2 tablet once a day | 1 tablet twice a day
children under 2 years | ask a doctor | ask a doctor

Other information

- Each tablet contains: Calcium 30 mg, Sodium 6 mg LOW SODIUM
- Store at 25°C (77°F); excursions permitted between 15°-30°C (59°-86°F)

Inactive ingredients

croscarmellose sodium, dibasic calcium phosphate dihydrate, microcrystalline cellulose, pregelatinized starch, colloidal silicon dioxide, magnesium stearate, polyvinyl alcohol, titanium dioxide, polyethylene glycol (PEG) 3350, talc, FD&C red 40 lake, FD&C yellow 5 lake

Principal Display Panel

NDC 63561-0187-01

Senna-S

DOCUSATE SODIUM 50 mg / STOOL SOFTENER

SENNOSIDES 8.6 mg / LAXATIVE

Compare to Senokot-S ®Dual Action Active Ingredients

100 Film-Coated Tablets

NDC 63561-0187-02

Senna-S

DOCUSATE SODIUM 50 mg / STOOL SOFTENER

SENNOSIDES 8.6 mg / LAXATIVE

Compare to Senokot-S ®Dual Action Active Ingredients

220 Film-Coated Tablets

NDC 63561-0187-03

Senna-S

DOCUSATE SODIUM 50 mg / STOOL SOFTENER

SENNOSIDES 8.6 mg / LAXATIVE

Compare to Senokot-S ®Dual Action Active Ingredients

1000 Film-Coated Tablets